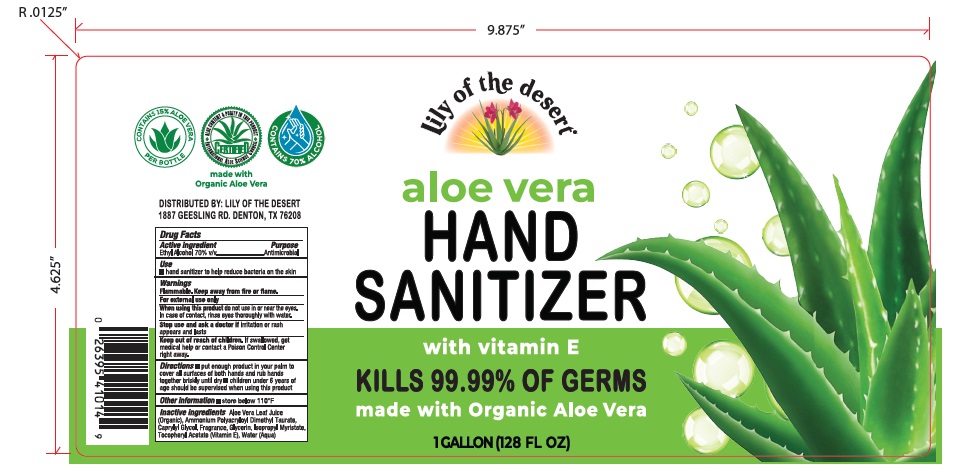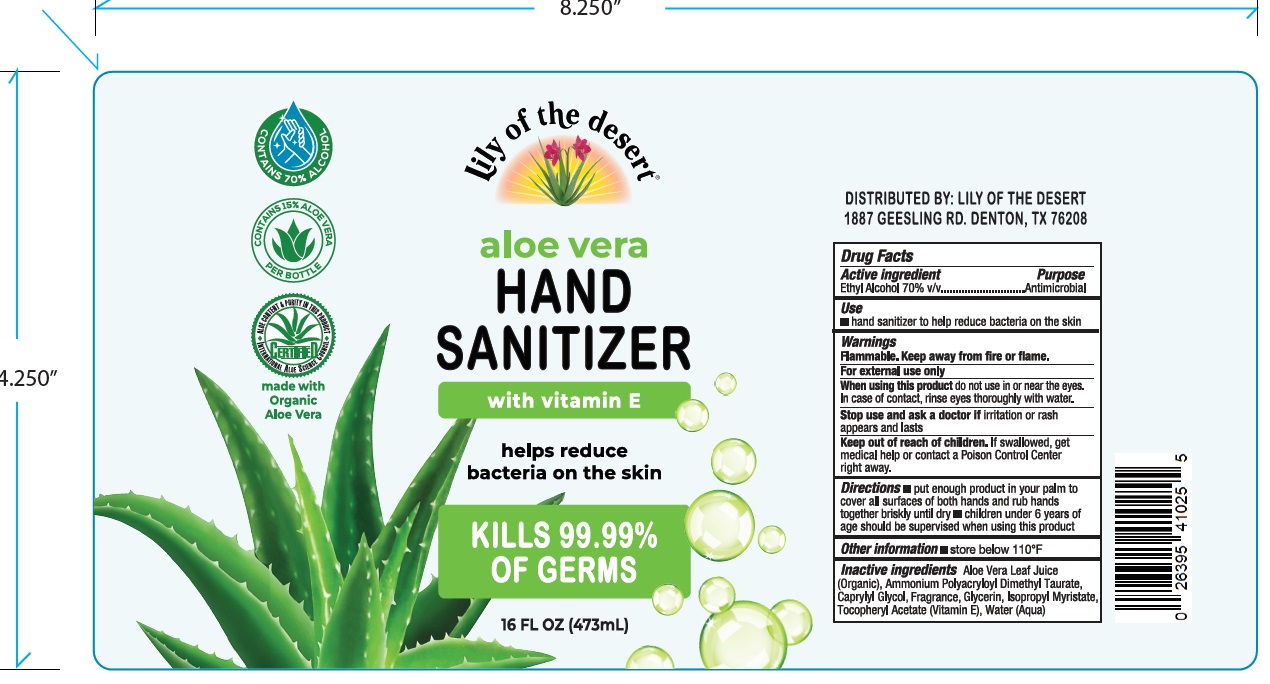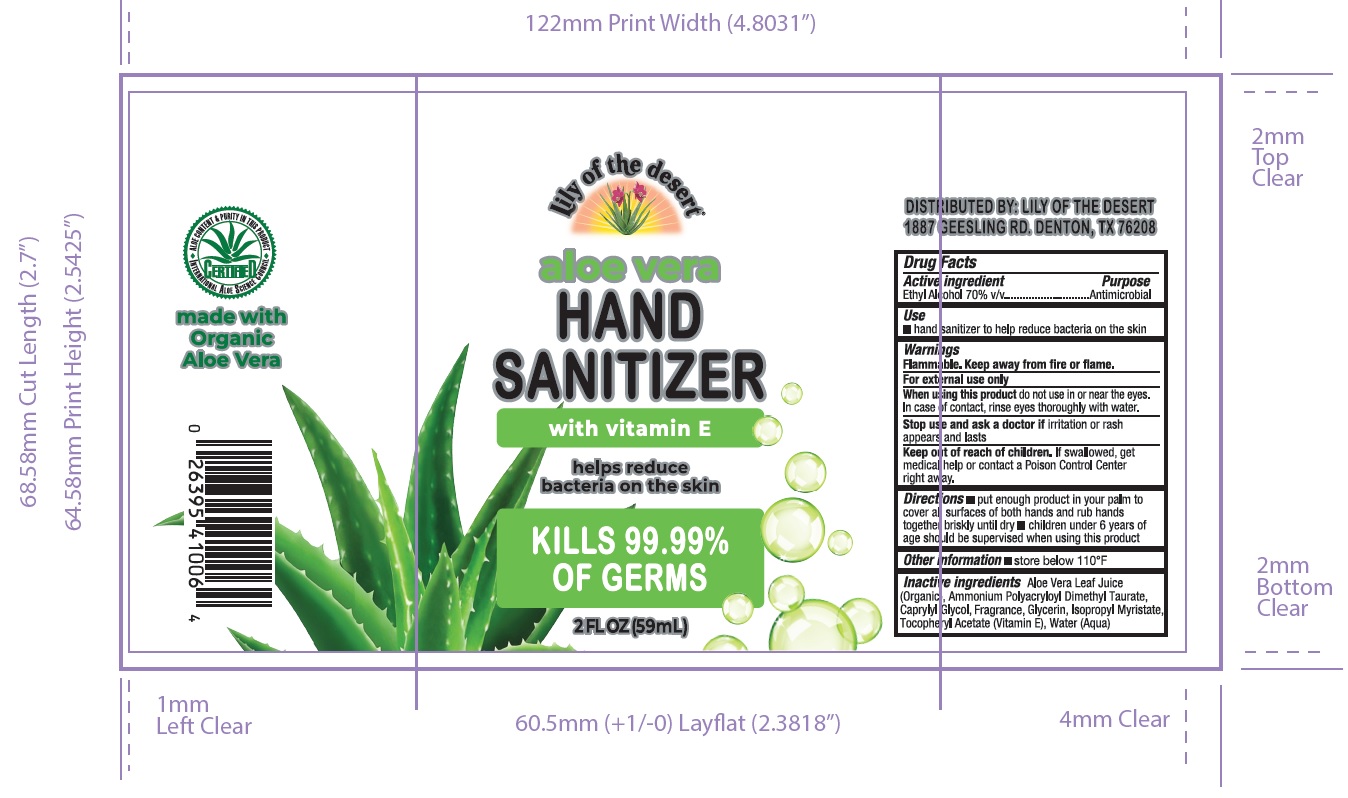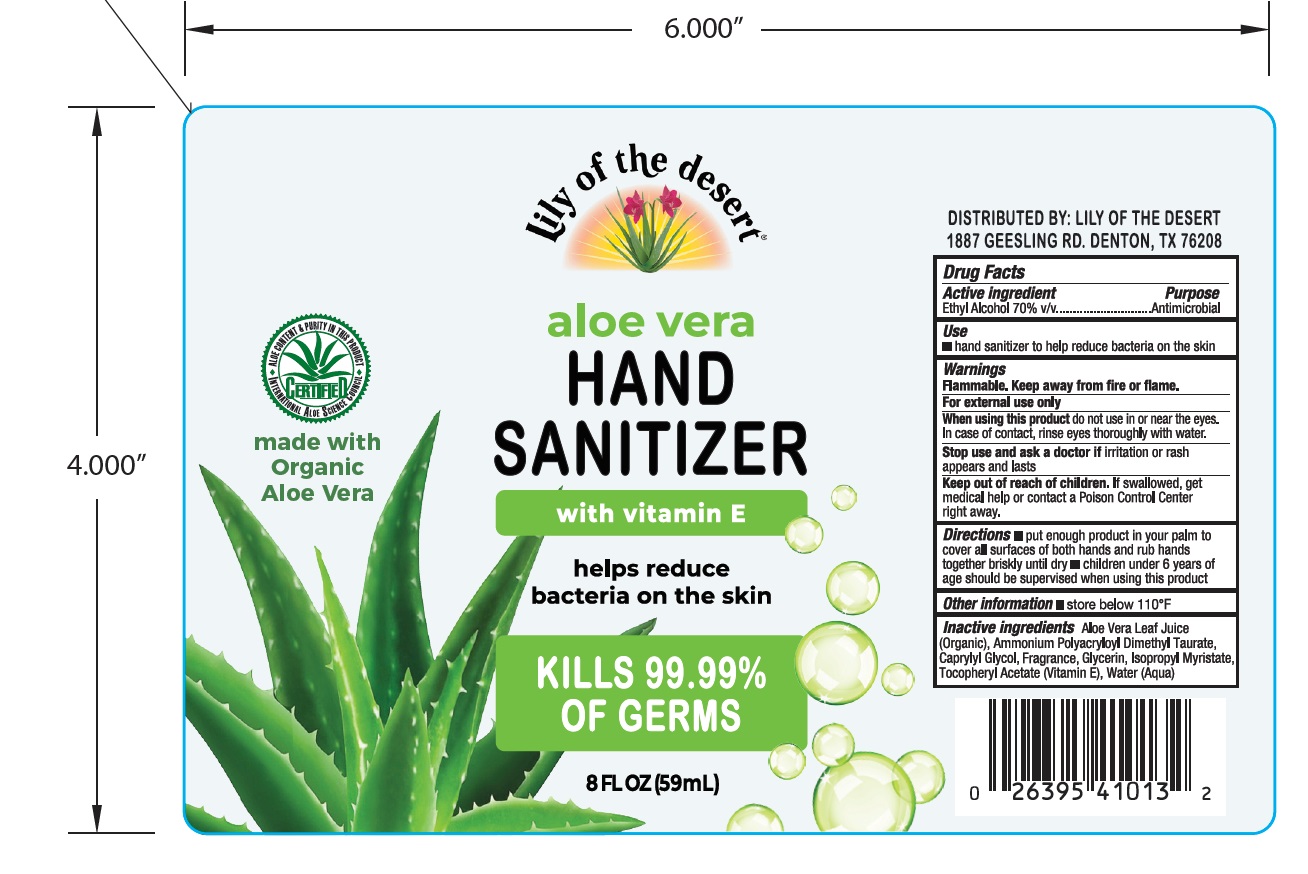 DRUG LABEL: Aloe Vera Hand Sanitizer w/Fragrance
NDC: 79949-001 | Form: GEL
Manufacturer: L.O.D.C. Group, Ltd.
Category: otc | Type: HUMAN OTC DRUG LABEL
Date: 20210713

ACTIVE INGREDIENTS: ALCOHOL 34.6231 g/51.3338 g
INACTIVE INGREDIENTS: GLYCERIN 0.37263 g/51.3338 g; ALOE VERA LEAF 8.87207 g/51.3338 g; WATER 6.38414 g/51.3338 g; CAPRYLYL GLYCOL 0.2703 g/51.3338 g; AMMONIUM POLYACRYLOYLDIMETHYL TAURATE (55000 MPA.S) 0.64167 g/51.3338 g; ISOPROPYL MYRISTATE 0.12053 g/51.3338 g; .ALPHA.-TOCOPHEROL ACETATE, DL- 0.02819 g/51.3338 g

Purpose

Hand sanitizer to help reduce bacteria on the skin

Use

hand sanitizer to help reduce bacteria on the skin

Warnings

Flammable. Keep away from heat or flame.

For external use only.

When using this product do not use in or near the eyes. In case of contact with eyes, rinse eyes thoroughly with water.
Stop use and ask a doctor if irritation or rash appears and lasts..
Keep out of reach of children. If swallowed, get medical help or contact a Poison Control Center right away.

Stop use and ask a doctor if irritation or rash appears and lasts.

Keep out of reach of children. If swallowed, get medical help or contact a Poison Control Center right away.

Directions

- Put enought product in your palm to cover all surfaces of both hands and rub hands together briskly until dry.
- children under 6 years of age should be supervised when using this product.

Other information

- Store below 110F

Inactive ingredients

Aloe Vera Leaf Juice (Organic), Ammonium Polyacryloyl Dimethyl Taurate, Caprylyl Glycol, Fragrance, Glycerin, Isopropyl Myristate, Tocopheryl Acetate (Vitamin E), Water (Aqua)

Active Ingredient(s)

Ethyl Alcohol 70% v/v. Purpose: Antiseptic

RECENT MAJOR CHANGES

Initial issue